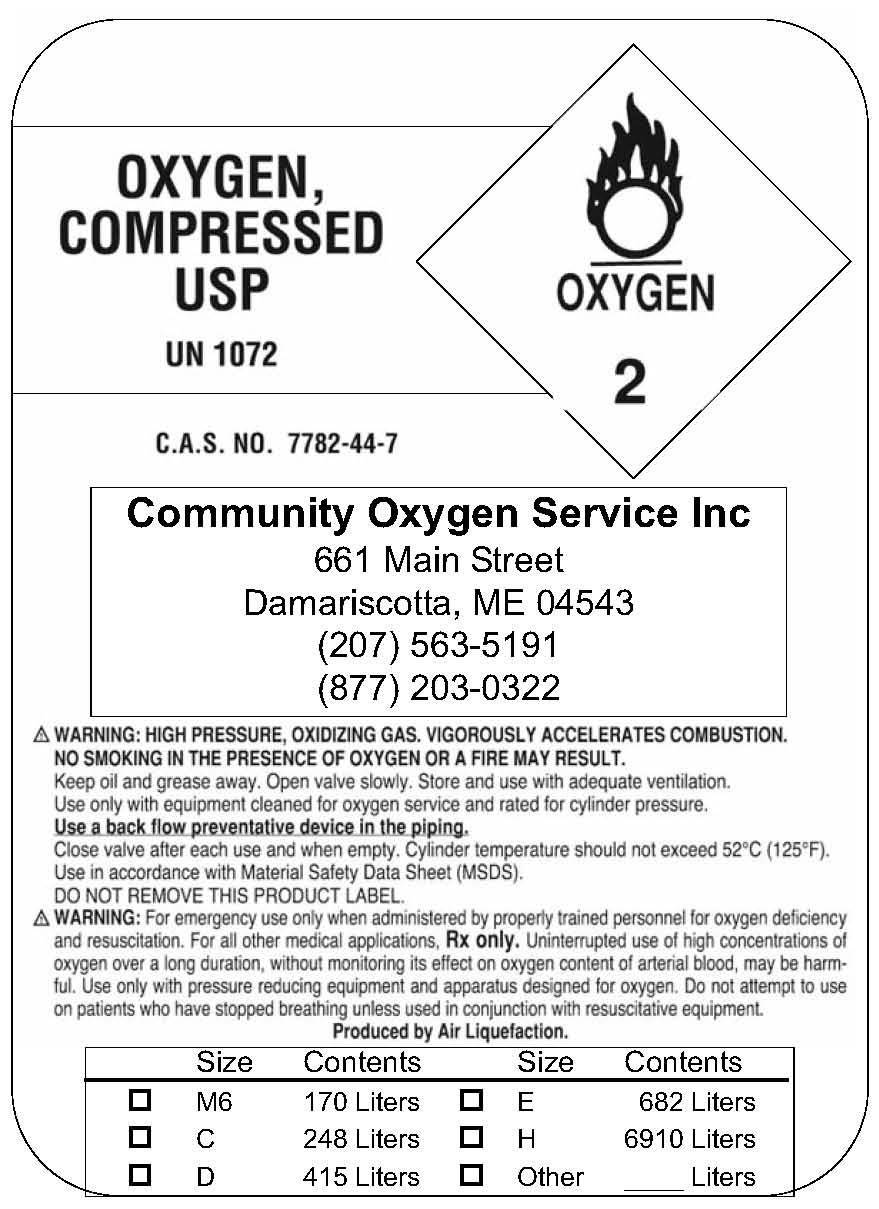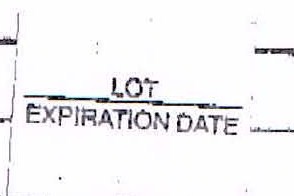 DRUG LABEL: Oxygen
NDC: 15240-0001 | Form: GAS
Manufacturer: Community Oxygen Services
Category: prescription | Type: HUMAN PRESCRIPTION DRUG LABEL
Date: 20100111

ACTIVE INGREDIENTS: Oxygen 99 L/100 L

Oxygen